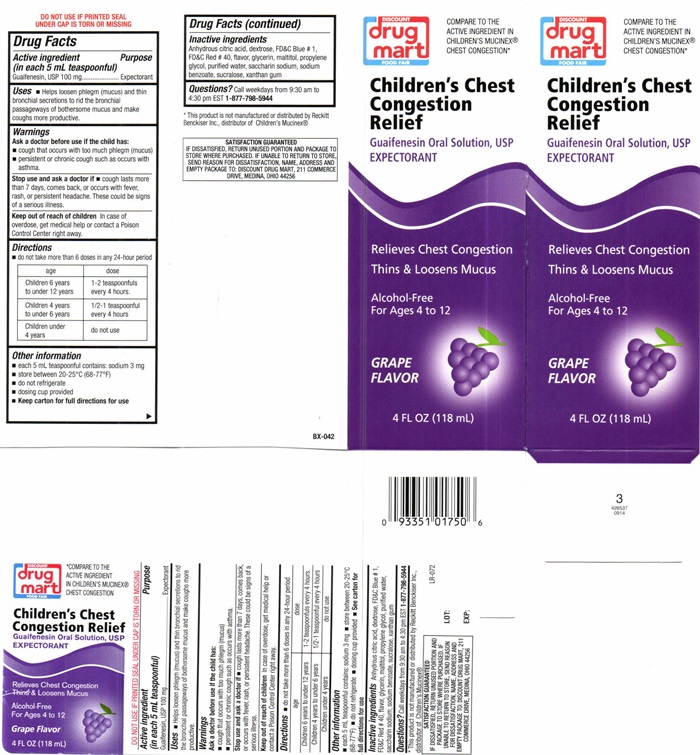 DRUG LABEL: Childrens Chest Congestion Relief Grape
NDC: 53943-511 | Form: LIQUID
Manufacturer: Discount Drug Mart
Category: otc | Type: HUMAN OTC DRUG LABEL
Date: 20251223

ACTIVE INGREDIENTS: GUAIFENESIN 100 mg/5 mL
INACTIVE INGREDIENTS: ANHYDROUS CITRIC ACID; DEXTROSE; FD&C BLUE NO. 1; FD&C RED NO. 40; GLYCERIN; MALTITOL; PROPYLENE GLYCOL; WATER; SACCHARIN SODIUM; SODIUM BENZOATE; SUCRALOSE; XANTHAN GUM

Drug Facts Active ingredient (in each 5 mL teaspoonful)

Guaifenesin, USP 100 mg

Purpose

Expectorant

Keep out of reach of children. In case of overdose, get medical help or contact a Poison Control Center right away.

Uses

- Helps loosen phlegm (mucus) and thin bronchial secretions to rid the bronchial passageways of bothersome mucus and make coughs more productive.

Warnings

DO NOT USE IF PRINTED SEAL UNDER CAP IS TORN OR MISSING.

Ask a doctor before use if the child has:

- cough that occurs with too much phlegm (mucus)
- persistant or chronic cough such as occurs with asthma.

Stop use and as a doctor if

- cough lasts more than 7 days, comes back, or occurs with fever, rash, or persistant headache. These could be signs of a serious illness

Directions

- do not use more than 6 doses in any 24-hour period

age | dose
Children 6 years to under 12 years | 1 - 2 teaspoonfuls every 4 hours
Children 4 years to under 6 years | 1/2 - 1 teaspoonful every 4 hours
Children under 4 years | do not use

Other information

- each 5 mL teaspoon contains: sodium 3 mg
- store at 20°-25°C (68°-77°F)
- do not refrigerate
- dosing cup provided
- Keep carton for full Directions for use.

Inactive ingredients

Anhydrous citric acid, dextrose, FD and C Blue # 1, FD and C Red # 40, flavor, glycerin, maltitol, propylene glycol, purified water, saccharin sodium, sodium benzoate, sucralose, xanthan gum

Questions?

Call weekdays from 9:30 AM to 4:30 PM EST at 1-877-798-5944

DISCOUNT drug mart FOOD FAIR Childrens Chest Congestion Relief - Grape

COMPARE TO THE ACTIVE INGREDIENT IN CHILDREN'S MUCINEX® CHEST CONGESTION

DISCOUNT

drug

mart

FOOD FAIR

Children's Chest Congestion Relief

Guaifenesin Oral Solution, USP

EXPECTORANT

Relieves Chest Congestion

Thins & Loosens Mucus

Alcohol-Free

For Ages 4 to 12

Grape Flavor

4 FL OZ (118 mL)

* This product is not manufactured or distributed by Reckitt Benckiser, Inc., distributer of Children's Mucinex®

SATISFACTION GUARANTEED
IF DISSASIFIED , RETURN UNUSED PORTION AND PACKAGE TO STORE WHERE PURCHASED. IF UNABLE TO RETURN TO STORE, SEND REASON FOR DISSATISFACTION, NAME, ADDRESS AND EMPTY PACKAGE TO: DISCOUNT DRUG MART, 211 COMMERCE DRIVE, MEDINA, OHIO 44256

res